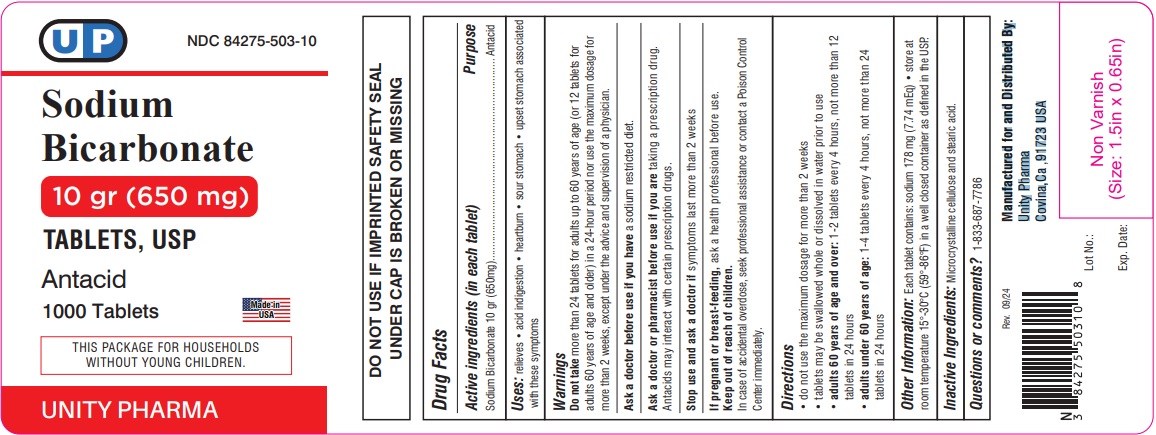 DRUG LABEL: Sodium Bicarbonate

NDC: 84275-503 | Form: TABLET
Manufacturer: Unity Pharma
Category: otc | Type: HUMAN OTC DRUG LABEL
Date: 20250423

ACTIVE INGREDIENTS: SODIUM BICARBONATE 650 mg/1 1
INACTIVE INGREDIENTS: STEARIC ACID; CELLULOSE, MICROCRYSTALLINE

Sodium Bicarbonate Tablets, USP 10gr (650 mg)

Drug Facts

Active ingredient (in each tablet)

Sodium Bicarbonate 10 gr (650 mg)

Purpose

Antacid

Uses

relieves:

- acid indigestion
- heartburn
- sour stomach
- upset stomach associated with these symptoms

Warnings

Do not takemore than 24 tablets for adults up to 60 years of age (or 12 tablets for adults 60 years of age and older) in a 24-hour period nor use the maximum dosage for more than 2 weeks, except under the advice and supervision of a physician.

Ask a doctor before use if you havea sodium restricted diet.

Ask a doctor or pharmacist before use if you aretaking a prescription drug.

Antacids may interact with certain prescription drugs.

Stop use and ask a doctor ifsymptoms last more than 2 weeks.

PREGNANCY OR BREAST FEEDING

If pregnant or breast-feeding, ask a health professional before use.

Keep out of reach of children.

OVERDOSAGE

In case of accidental overdose, seek professional assistance or contact a Poison Control Center immediately.

Directions

- do not use the maximum dosage for more than 2 weeks
- tablets may be swallowed whole or dissolved in water prior to use
- adults 60 years of age and over:1-2 tablets every 4 hours, not more than 12 tablets in 24 hours
- adults under 60 years of age:1-4 tablets every 4 hours, not more than 24 tablets in 24 hours

Other information

each tablet contains: sodium 178 mg (7.74 mEq)

store at room temperature 15º - 30º C (59º - 86º F) in a well closed container as defined in the USP

Inactive ingredients

Microcrystalline cellulose and stearic acid

Questions or comments?

1-833-687-7786

Manufactured for and Distributed By:

Unity Pharma

Covina, Ca 91723 USA

Rev. 09/24

PACKAGE LABEL

Unity Pharma

NDC: 84275-503-10

Sodium Bicarbonate Tablets, USP 10 gr (650 mg)

ANTACID

1000 Tablets